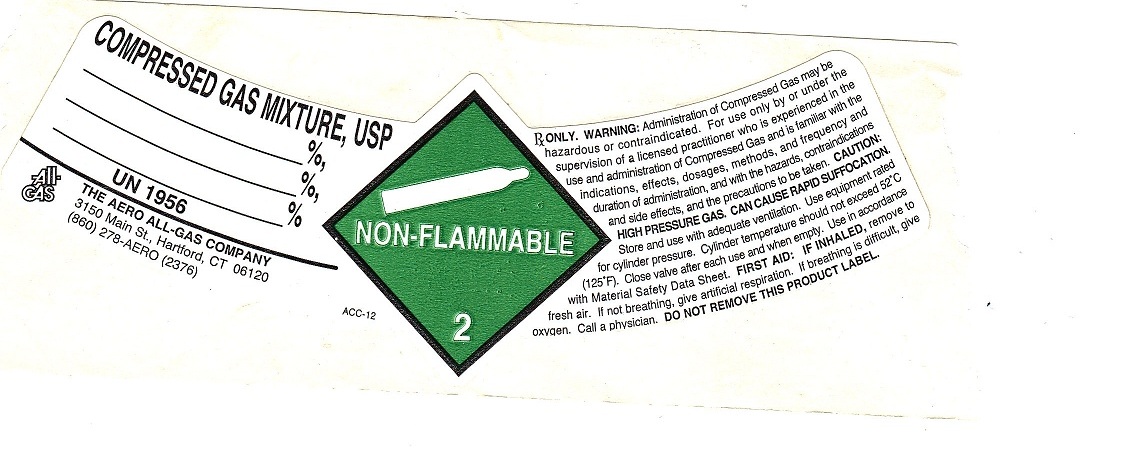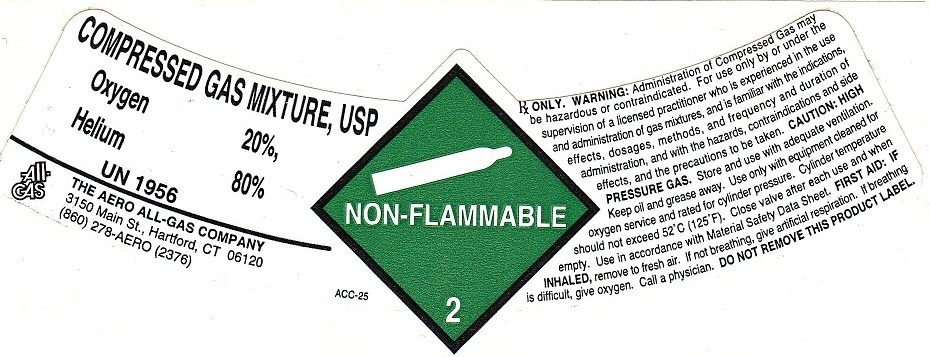 DRUG LABEL: Oxygen Helium Mixture
NDC: 10014-006 | Form: GAS
Manufacturer: Aero All Gas Company
Category: prescription | Type: HUMAN PRESCRIPTION DRUG LABEL
Date: 20100525

ACTIVE INGREDIENTS: Oxygen 200 mL/1 L; Helium 800 mL/1 L

O2 20 HE 80 MIX

PACKAGE LABEL

COMPRESSED GAS MIXTURE, USP %, %, % UN1956
ALL-GAS THE AERO ALL-GAS COMPANY 3150 Main St. Hartford, CT 06120 (860) 278-AERO (2376)
ACC-12
NON-FLAMMABLE GAS 2
Rx only. WARNING: Administration of Compressed Gas may be hazardous or contraindicated. For use only by or under the supervision of a licensed practitioner who is experienced in the use administration of Compressed Gas and is familiar with the indications, effects, dosages, methods, and frequency and duration of administration, and with the hazards, contraindications and side effects and the precautions to be taken. WARNING: HIGH PRESSURE GAS. CAN CAUSE RAPID SUFFOCATION. Store and use with adequate ventilation. Use equipment rated for cylinder pressure. Cylinder temperature should not exceed 52C (125F). Use in accordance with the Material Safety Data Sheet (MSDS).
FIRST AID: IF INHALED, remove to fresh air. If not breathing, give artificial respiration. If breathing is difficult, give oxygen. Call a physician. DO NOT REMOVE THIS PRODUCT LABEL.

PACKAGE LABEL

COMPRESSED GAS MIXTURE, USP OXYGEN 20% HELIUM 80% UN1956
ALL-GAS THE AERO ALL-GAS COMPANY 3150 Main St. Hartford, CT 06120 (860) 278-AERO (2376)
ACC-25
NON-FLAMMABLE 2
Rx only. WARNING: Administration of Compressed Gas may be hazardous or contraindicated. For use only by or under the supervision of a licensed practitioner who is experienced in the use administration of Nitrogen and is familiar with the indications, effects, dosages, methods, and frequency and duration of administration, and with the hazards, contraindications and side effects and the precautions to be taken. WARNING: HIGH PRESSURE GAS. Store and use with adequate ventilation. Keep oil and grease away. Use only with equipment cleaned for Oxygen service and rated for cylinder pressure. Cylinder temperature should not exceed 52C (125F). Close valve after each use and when empty. Use in accordance with the Material Safety Data Sheet.
FIRST AID: IF INHALED, remove to fresh air. If not breathing, give artificial respiration. If breathing is difficult, give oxygen. Call a physician. DO NOT REMOVE THIS PRODUCT LABEL.